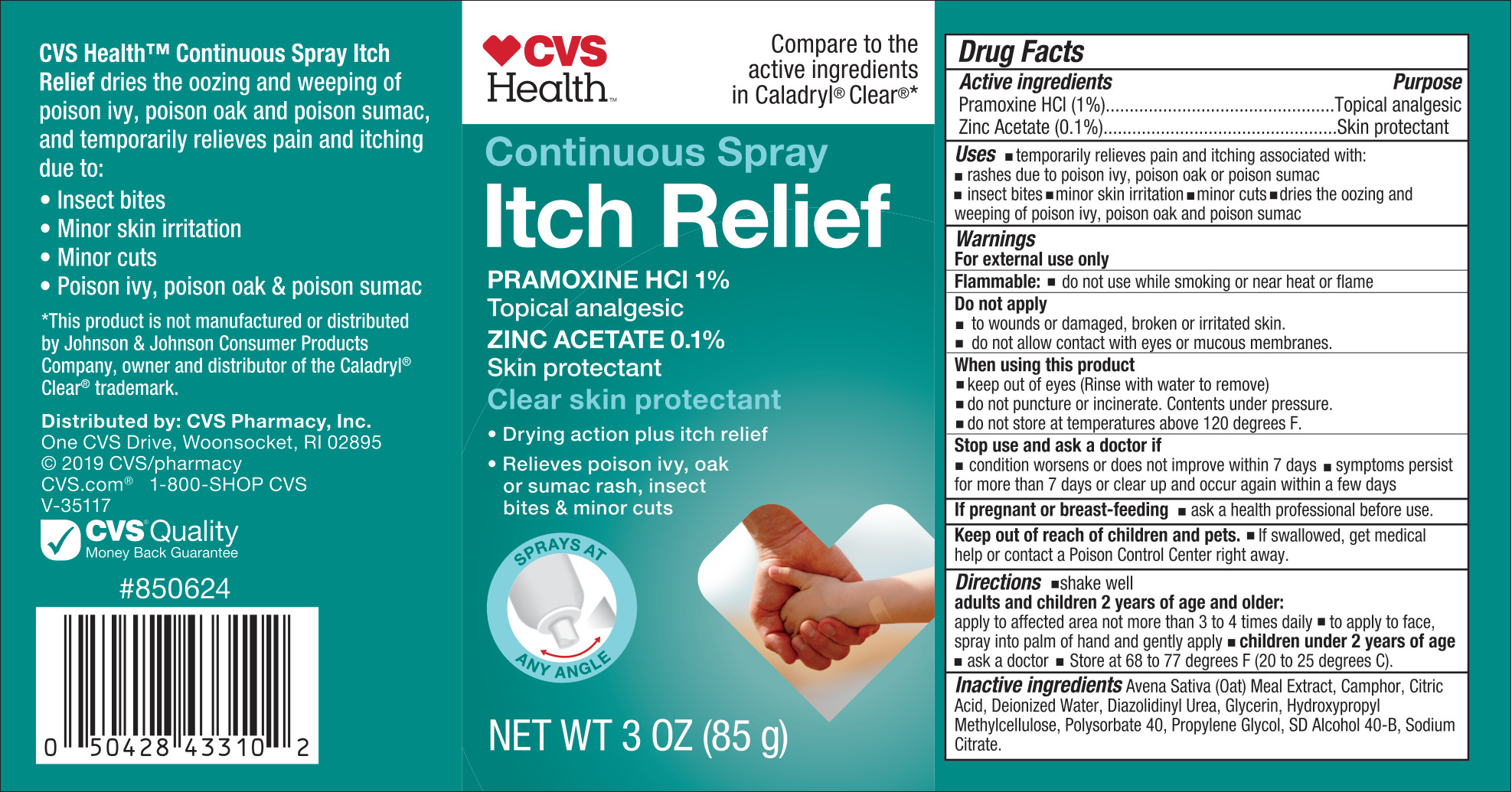 DRUG LABEL: CVS Itch Relief
NDC: 51316-624 | Form: SPRAY
Manufacturer: CVS Pharmacy
Category: otc | Type: HUMAN OTC DRUG LABEL
Date: 20251222

ACTIVE INGREDIENTS: PRAMOXINE HYDROCHLORIDE 10 mg/1 g; ZINC ACETATE DIHYDRATE 1 mg/1 g
INACTIVE INGREDIENTS: ANHYDROUS CITRIC ACID; SODIUM CITRATE; CAMPHOR (SYNTHETIC); OATMEAL; WATER; ALCOHOL; GLYCERIN; POLYSORBATE 40; PROPYLENE GLYCOL; DIAZOLIDINYL UREA; HYDROXYPROPYL METHYLCELLULOSE

CVS Itch Relief

Active ingredients

Pramoxine HCl 1%

Zinc Acetate 0.1%

Purposes

Topical analgesic

Skin protectant

Uses

- temporarily relieves pain and itching associated with:
- rashes due to posion ivy, poison oak or poison sumac
- insect bites
- minor skin irritation
- minor cuts
- dries the oozing and weeping of poison ivy, poison oak and poison sumac

Warnings

For external use only

Flammable: Do not use while smoking or near heat or flame

Do not apply

- to wounds or damaged, broken or irritated skin.
- do not allow contact with eyes or mucous membranes.

When using this product

- keep out of eyes (Rinse with water to remove)
- do not puncture or incinerate. Contents under pressure.
- do not store at temperatures above 120 degrees F.

Stop use and ask a doctor if

- condition worsens or does not improve within 7 days
- symptoms persist for more than 7 days or clear up and occur again within a few days

If pregnant or breast-feeding

- ask a health professional before use.

Keep out of reach of children and pets.

If swallowed, get medical help or contact a Poison Control Center right away.

Directions

- shake well
- adults and children 2 years of age and older:
- apply to affected area not more than 3 to 4 times daily
- to apply to face, spray into palm of hand and gently apply
- children under 2 years of age
- ask a doctor
- Store at 68 to 77 degrees F (20 to 25 degrees C).

Inactive ingredients

Avena Sativa (Oat) Meal Extract, Camphor, Citric Acid, Deionized Water, Diazolidinyl Urea, Glycerin, Hydroxypropyl Methylcellulose, Polysorbate 40, Propylene Glycol, SD Alcohol 40-B, Sodium Citrate

PACKAGE LABEL

CVS HealthTM

Compare to the active ingredients in Caladryl® Clear®*

Continuous Spray

Itch Relief

Pramoxine HCl 1%

Topical analgesic

Zinc Acetate 0.1%

Skin protectant

Clear skin protectant

- Drying action plus itch relief
- Relieves poison ivy, oak or sumac rash, insect bites & minor cuts

Sprays at any angle

NET WT 3 OZ (85 g)